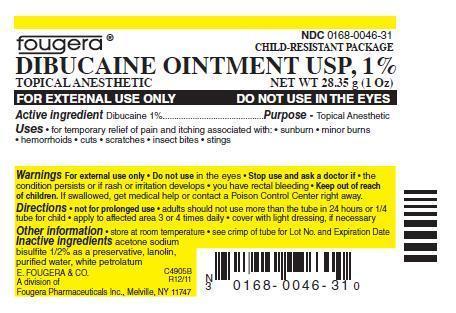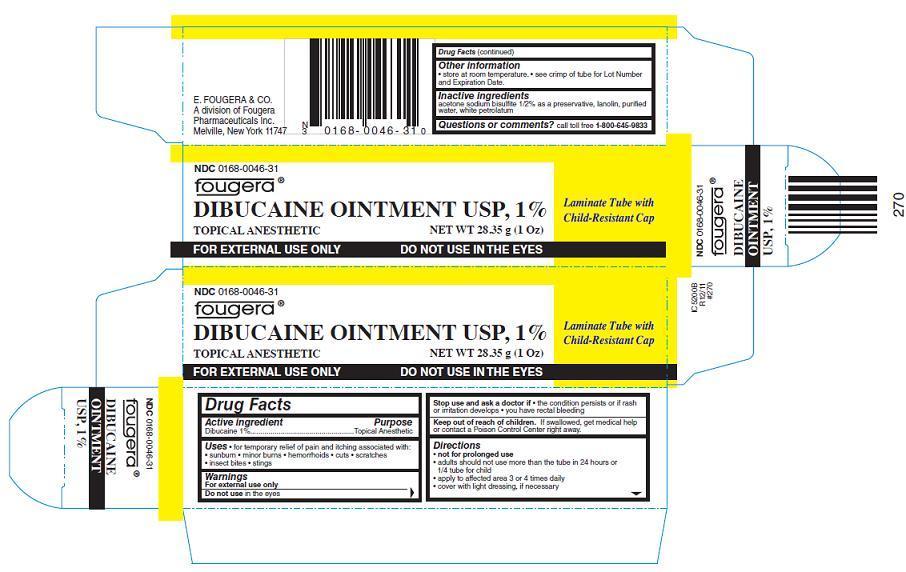 DRUG LABEL: DIBUCAINE
NDC: 0168-0046 | Form: OINTMENT
Manufacturer: E. Fougera & Co. a division of Fougera Pharmaceuticals Inc.
Category: otc | Type: HUMAN OTC DRUG LABEL
Date: 20120725

ACTIVE INGREDIENTS: DIBUCAINE 1 g/100 g
INACTIVE INGREDIENTS: ACETONE SODIUM BISULFITE; LANOLIN; PETROLATUM; WATER

DIBUCAINE OINTMENT USP, 1%

Active Ingredient:

Dibucaine 1%

Purpose:

Topical Anesthetic

Uses:

- for temporary relief of pain and itching associated with:
- sunburn
- minor burns
- hemorrhoids
- cuts
- scratches
- insect bites
- stings

Warnings:

For external use only

Do not use in the eyes

Stop use and ask a doctor if

- the condition persists or if rash or irritation develops
- you have rectal bleeding

Keep out of reach of children.

If swallowed, get medical help or contact a Poison Control Center right away.

Directions:

- not for prolonged use
- adults should not use more than the tube in 24 hours or 1/4 tube for child
- apply to affected area 3 or 4 times daily
- cover with light dressing, if necessary

Other information:

- store at room temperature.
- see crimp of tube for Lot Number and Expiration Date.

Inactive Ingredients

acetone sodium bisulfite 1/2% as a preservative, lanolin, purified water, white petrolatum

Questions or comments? call toll free 1-800-645-9833

E. FOUGERA & CO.

A division of Fougera Pharmaceuticals Inc.

Melville, NY 11747

C4905B

R12/11

PACKAGE LABEL – PRINCIPAL DISPLAY PANEL – CONTAINER

Fougera®

NDC 0168-0046-31

CHILD-RESISTANT PACKAGE

DIBUCAINE OINTMENT USP, 1%

TOPICAL ANESTHETIC

NET WT 28.35g (1 Oz)

FOR EXTERNAL USE ONLY

DO NOT USE IN THE EYES

PACKAGE LABEL – PRINCIPAL DISPLAY PANEL – CARTON

NDC 0168-0046-31

Fougera®

DIBUCAINE OINTMENT USP, 1%

TOPICAL ANESTHETIC

NET WT 28.35g (1 Oz)

Laminate Tube with Child-Resistant Cap

FOR EXTERNAL USE ONLY

DO NOT USE IN THE EYES